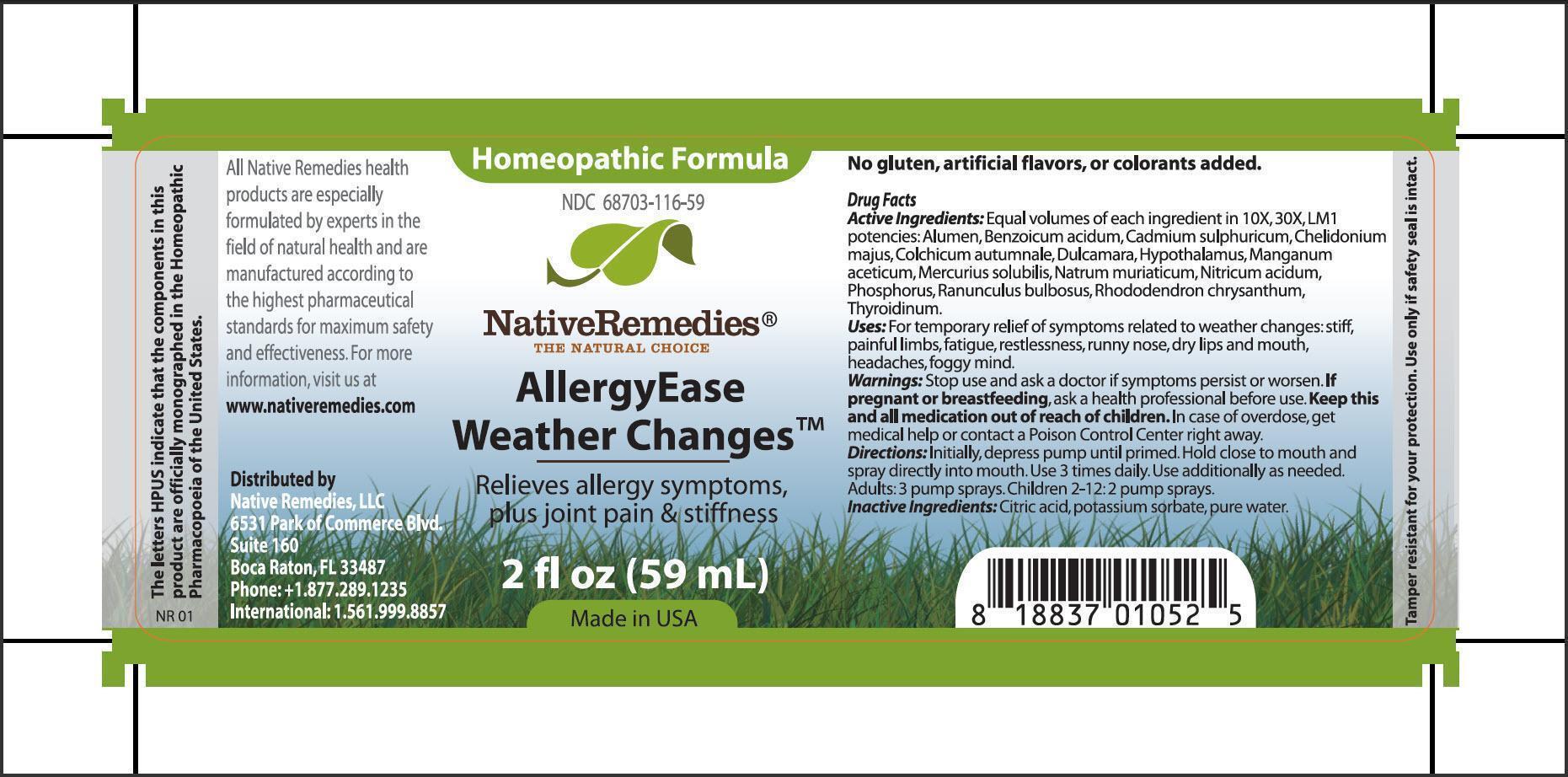 DRUG LABEL: AllergyEase Weather Changes
NDC: 68703-116 | Form: SPRAY
Manufacturer: Native Remedies, LLC
Category: homeopathic | Type: HUMAN OTC DRUG LABEL
Date: 20130724

ACTIVE INGREDIENTS: POTASSIUM ALUM 10 [hp_X]/59 mL; BENZOIC ACID 10 [hp_X]/59 mL; CADMIUM SULFATE 10 [hp_X]/59 mL; CHELIDONIUM MAJUS 10 [hp_X]/59 mL; COLCHICUM AUTUMNALE BULB 10 [hp_X]/59 mL; SOLANUM DULCAMARA TOP 10 [hp_X]/59 mL; BOS TAURUS HYPOTHALAMUS 10 [hp_X]/59 mL; MANGANESE ACETATE TETRAHYDRATE 10 [hp_X]/59 mL; MERCURIUS SOLUBILIS 10 [hp_X]/59 mL; SODIUM CHLORIDE 10 [hp_X]/59 mL; NITRIC ACID 10 [hp_X]/59 mL; PHOSPHORUS 10 [hp_X]/59 mL; RANUNCULUS BULBOSUS 10 [hp_X]/59 mL; RHODODENDRON AUREUM LEAF 10 [hp_X]/59 mL; THYROID, UNSPECIFIED 10 [hp_X]/59 mL
INACTIVE INGREDIENTS: CITRIC ACID MONOHYDRATE; POTASSIUM SORBATE; WATER

AllergyEase Weather Changes

PURPOSE

Relieves allergy symptoms, plus joint pain and stiffness

Drug Facts
Active Ingredients: Equal volumes of each ingredient in 10X, 30X, LM1 potencies: Alumen, Benzoicum acidum, Cadmium sulphuricum, Chelidonium majus, Colchicum autumnale, Dulcamara, Hypothalamus, Manganum aceticum, Mercurius solubilis, Natrum muriaticum, Nitricum acidum, Phosphorus, Ranunculus bulbosus, Rhododendron chrysanthum, Thyroidinum

INDICATIONS AND USAGE

Uses:For temporary relief of symptoms related to weather changes: stiff, painful limbs, fatigue, restlessness, runny nose, dry lips and mouth, headaches, foggy mind

WARNINGS

Warnings: Stop use and ask a doctor if symptoms persist or worsen

PREGNANCY OR BREAST FEEDING

If pregnant or breastfeeding, ask a health professional before use

KEEP OUT OF REACH OF CHILDREN

Keep this and all medication out of reach of children

OVERDOSAGE

In case of overdose, get medical help or contact a Poison Control Center right away

DOSAGE AND ADMINISTRATION

Directions: Initially, depress pump until primed. Hold close to mouth and spray directly into mouth. Use 3 times daily. Use additionally as needed. Adults: 3 pump sprays. Children 2-12: 2 pumps sprays

Inactive Ingredients: Citric acid, potassium sorbate, pure water

PATIENT COUNSELING INFORMATION

The letters HPUS indicate that the components in this product are officially monographed in the Homeopathic Pharmacopoeia of the United States

All Native Remedies health products are especially formulated by experts in the field of natural health and are manufactured according to the highest pharmaceutical standards for maximum safety and effectiveness. For more information, visit us at www.nativeremedies.com

Distributed by
Native Remedies, LLC
6531 Park of Commerce Blvd.
Suite 160
Boca Raton, FL 33487
Phone: +1.877.289.1235
International: 1.561.999.8857

No gluten, artificial flavors, or colorants added

STORAGE AND HANDLING

Tamper resistant for your protection. Use only if safety seal is intact